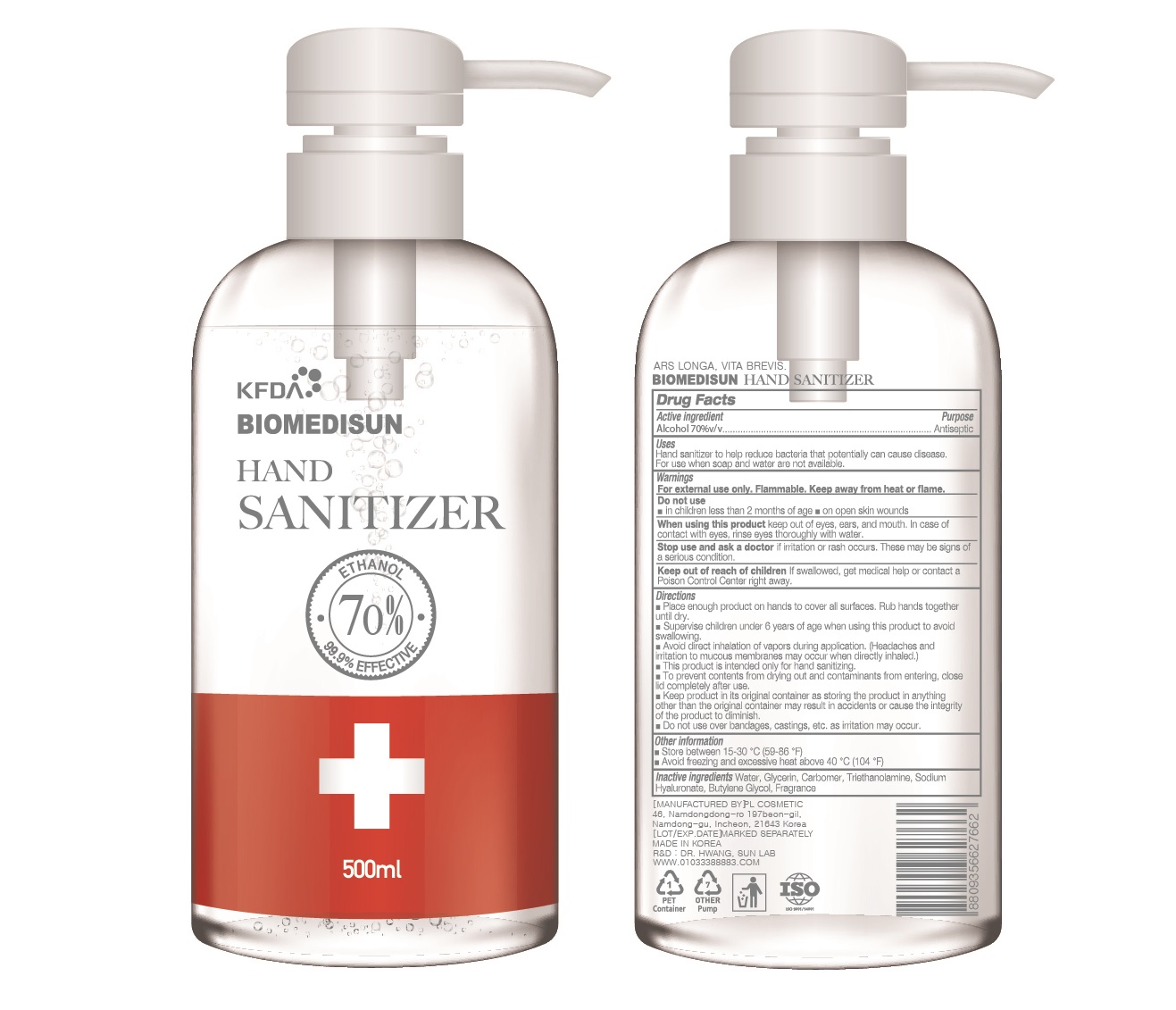 DRUG LABEL: BIOMEDISUN HAND SANITIZER
NDC: 74339-3570 | Form: GEL
Manufacturer: PL COSMETIC
Category: otc | Type: HUMAN OTC DRUG LABEL
Date: 20200406

ACTIVE INGREDIENTS: ALCOHOL 350 mL/500 mL
INACTIVE INGREDIENTS: GLYCERIN; CARBOMER HOMOPOLYMER, UNSPECIFIED TYPE; WATER; BUTYLENE GLYCOL; HYALURONATE SODIUM; TROLAMINE

[BIOMEDISUN] 500 ml PUMP TYPE 70: 74339-3570